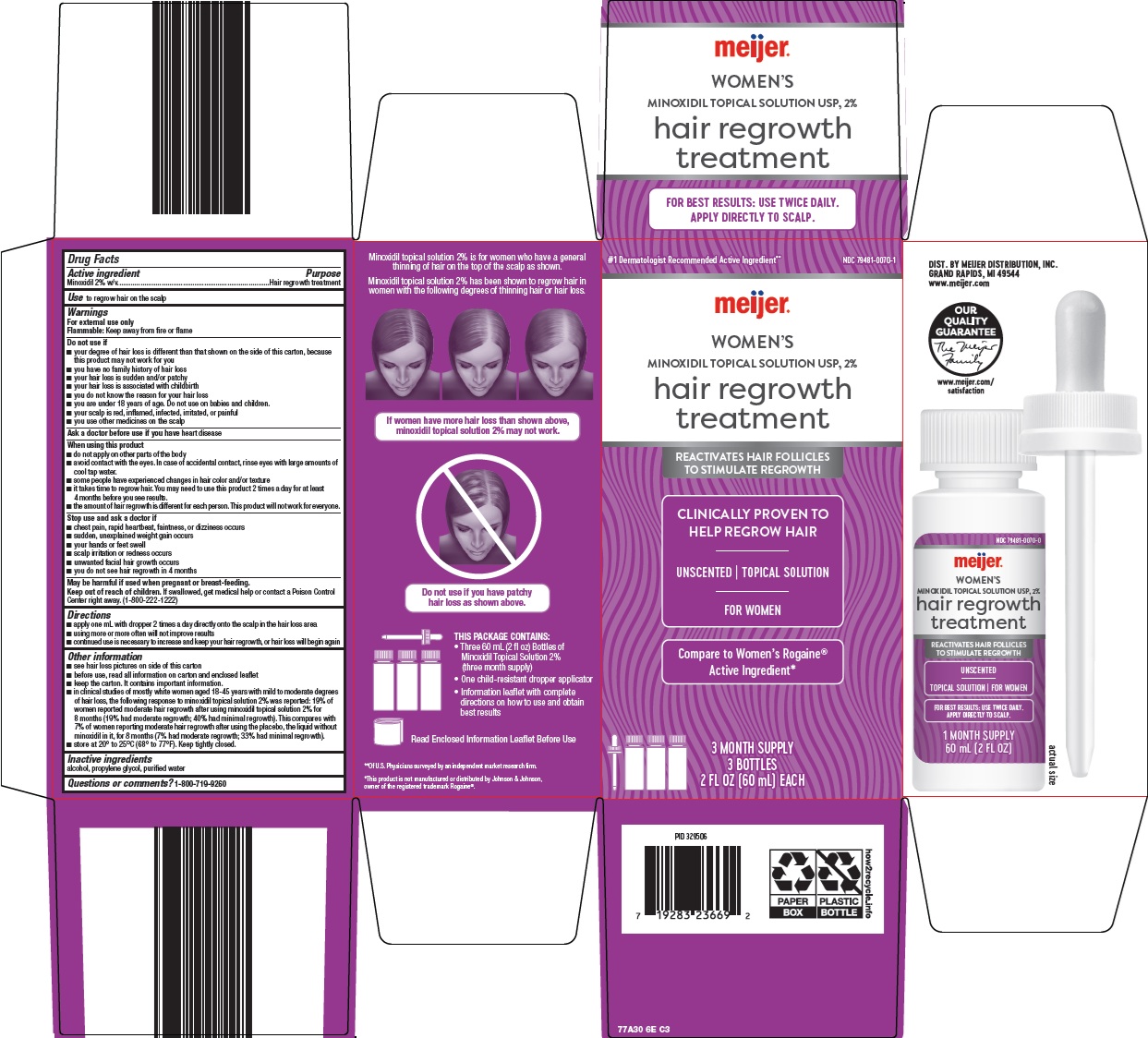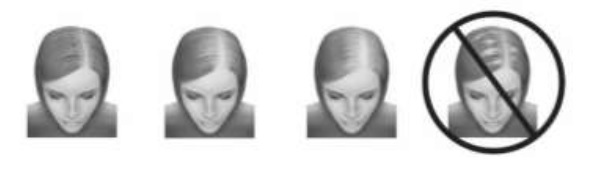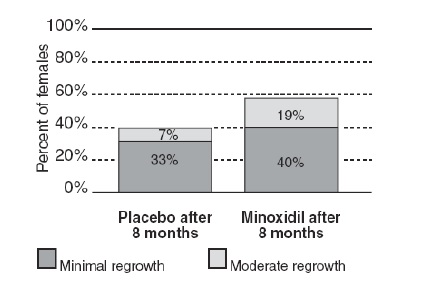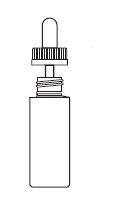 DRUG LABEL: hair regrowth treatment
NDC: 79481-0070 | Form: SOLUTION
Manufacturer: Meijer, Inc.
Category: otc | Type: HUMAN OTC DRUG LABEL
Date: 20260205

ACTIVE INGREDIENTS: MINOXIDIL 2 g/100 mL
INACTIVE INGREDIENTS: ALCOHOL; PROPYLENE GLYCOL; WATER

Meijer Distribution, Inc. Hair Regrowth Treatment Drug Facts

Active ingredient

Minoxidil 2% w/v

Purpose

Hair regrowth treatment

Use

to regrow hair on the scalp

Warnings

For external use only

Flammable: Keep away from fire or flame

Do not use if

- your degree of hair loss is different than that shown on the side of this carton, because this product may not work for you
- you have no family history of hair loss
- your hair loss is sudden and/or patchy
- your hair loss is associated with childbirth
- you do not know the reason for your hair loss
- you are under 18 years of age. Do not use on babies and children.
- your scalp is red, inflamed, infected, irritated, or painful
- you use other medicines on the scalp

Ask a doctor before use if you have

heart disease

When using this product

- do not apply on other parts of the body
- avoid contact with the eyes. In case of accidental contact, rinse eyes with large amounts of cool tap water.
- some people have experienced changes in hair color and/or texture
- it takes time to regrow hair. You may need to use this product 2 times a day for at least 4 months before you see results.
- the amount of hair regrowth is different for each person. This product will not work for everyone.

Stop use and ask a doctor if

- chest pain, rapid heartbeat, faintness, or dizziness occurs
- sudden, unexplained weight gain occurs
- your hands or feet swell
- scalp irritation or redness occurs
- unwanted facial hair growth occurs
- you do not see hair regrowth in 4 months

Keep out of reach of children.

If swallowed, get medical help or contact a Poison Control Center right away. (1-800-222-1222)

Directions

- apply one mL with dropper 2 times a day directly onto the scalp in the hair loss area
- using more or more often will not improve results
- continued use is necessary to increase and keep your hair regrowth, or hair loss will begin again

Other information

- see hair loss pictures on side of this carton
- before use, read all information on carton and enclosed leaflet
- keep the carton. It contains important information.
- in clinical studies of mostly white women aged 18-45 years with mild to moderate degrees of hair loss, the following response to minoxidil topical solution 2% was reported: 19% of women reported moderate hair regrowth after using minoxidil topical solution 2% for 8 months (19% had moderate regrowth; 40% had minimal regrowth). This compares with 7% of women reporting moderate hair regrowth after using the placebo, the liquid without minoxidil in it, for 8 months (7% had moderate regrowth; 33% had minimal regrowth).
- store at 20° to 25°C (68° to 77°F). Keep tightly closed.

Inactive ingredients

alcohol, propylene glycol, purified water

Questions or comments?

1-800-719-9260

Consumer Information

IMPORTANT INFORMATION ABOUT

Minoxidil Topical Solution USP 2%

Hair Regrowth Treatment

UNSCENTED

For Women

Over 30 million American women experience hair thinning or hair loss, so you're not alone. Minoxidil topical solution 2% contains the only ingredient that is medically proven effective to help regrow hair in women.

  - Clinically Proven to Help Regrow Hair
  - Reactivates Hair Follicles To Stimulate Regrowth
  - Previously Available Only by Prescription

SAVE THIS LEAFLET FOR FUTURE REFERENCE

Please read this leaflet carefully. It will help you understand how to use minoxidil topical solution 2% and what to expect from its use. If you have any questions after reading this leaflet, or anytime while using minoxidil topical solution 2%, you should ask your health care professional or call us at 1-800-719-9260.

What is minoxidil topical solution 2%?

Minoxidil topical solution 2% is a colorless liquid medication for use only on the top of the scalp to help regrow hair.

Who may use minoxidil topical solution 2%?

Minoxidil topical solution 2% may be appropriate for you if you are an adult who is at least 18 years old and experiencing gradually thinning hair or gradual hair loss on the top of the head. The common hereditary thinning or hair loss process begins slowly and may become noticeable only after years of gradual loss.

Minoxidil topical solution 2% is for general thinning of hair on the top of the scalp as shown below. Minoxidil topical solution 2% has been shown to regrow hair in women with the degrees of hair loss shown. If women have more hair loss than shown, minoxidil topical solution 2% may not work.

Many of those experiencing hair loss have other family members with gradual thinning hair or hair loss. If there is no family history of gradual thinning or gradual hair loss, or hair loss ispatchy, talk to your doctor.

Who should NOT use minoxidil topical solution 2%?

Minoxidil topical solution 2% will not prevent or improve hair loss related to pregnancy, the use of some prescription and non-prescription medications, certain severe nutritional problems (very low body iron; excessive vitamin A intake), the recently discontinued use of birth control pills, low thyroid states (hypothyroidism), chemotherapy, or diseases which cause scarring of the scalp. Also, minoxidil topical solution 2% will not improve hair loss due to:

- damage from the use of hair care products which cause scarring or deep burns of the scalp.
- hair grooming methods such as cornrowing or ponytails which require pulling the hair tightly back from the scalp.

Do not use minoxidil topical solution 2% if hair loss is patchy as shown below.

You should ask yourdoctor if you are unsure of the cause of your hair loss.

Will minoxidil topical solution 2% work for me?

The amount of hair regrowth is different for each person. Not everyone will respond to minoxidil topical solution 2%. The response to minoxidil topical solution 2% cannot be predicted. No one will be able to grow back all their hair.

In clinical studies of mostly white women aged 18-45 years with mild to moderate degrees of hair loss, the following response to minoxidil topical solution 2% was reported:

FEMALE RESPONSE TO MINOXIDIL TOPICAL SOLUTION 2%

Percent reporting hair regrowth

19% of women reported moderate hair regrowth after using minoxidil topical solution 2% for 8 months (19% had moderate regrowth; 40% had minimal regrowth). This compares with 7% of women reporting moderate hair regrowth after using the placebo, the liquid without minoxidil in it, for 8 months (7% had moderate regrowth; 33% had minimal regrowth).

What Minimal, Moderate and Dense Hair Regrowth Will Mean For You

Number of Hairs |  | Hair Density
Minimal | Some new hairs are seen, but not enough to cover thinning areas. | Hairs in thinning areas do not grow as closely together as hairs on the rest of the head.
Moderate | New hairs cover some or all of thinning areas. | Hairs in the thinning areas grow more closely together, but are not as close together as hairs on the rest of the head.
Dense | New hairs cover, or almost completely cover, thinning areas. | Hairs in thinning areas grow as closely together as hairs on the rest of the head.

Can minoxidil topical solution 2% be used to prevent hair loss?

We do not know if minoxidil topical solution 2% will prevent hair loss.

How soon can I expect results from using minoxidil topical solution 2%?

Since normal hair usually grows only 1/2 to 1 inch per month, hair regrowth with minoxidil topical solution 2% also takes time. Generally new hair growth is slow for a minoxidil topical solution 2% user. Continued use of 2 times a day for at least 4 months is usually needed before you notice hair regrowth.

If you do not see hair regrowth in 4 months, stop using minoxidil topical solution 2% and see your doctor.

When you first begin to use minoxidil topical solution 2%, your hair loss may continue for up to 2 weeks. This hair loss is temporary. If you continue to lose hair after two weeks, see your doctor.

If minoxidil topical solution 2% is working, what will the hair look like?

At first, hair growth may be soft, downy, colorless hairs. After further use, the new hairs should be the same color and thickness as the other hairs on your scalp.

How long do I need to use minoxidil topical solution 2%?

If you respond to minoxidil topical solution 2%, you will need to use it 2 times a day to keep and continue the hair regrowth. Up to 8 months of usage may be needed to see your best results from minoxidil topical solution 2%.

What happens if I completely stop using minoxidil topical solution 2%?

Will I keep the new hair?

Continuous use of minoxidil topical solution 2% is needed to maintain hair regrowth. If you stop using minoxidil topical solution 2%, the normal hair loss process will start again. You will probably lose your newly regrown hair in three to four months.

What is the dosage of minoxidil topical solution 2%?

You should apply a dose (1 mL) of minoxidil topical solution 2% directly onto the scalp in the hair loss area TWO TIMES A DAY; for example, once in the morning and once at night. Each bottle should last about one month, if used as directed. Please refer to the "Directions for Use" section of this leaflet.

What if I miss a dose or forget to use minoxidil topical solution 2%?

If you miss one or two daily doses of minoxidil topical solution 2%, just continue with your next dose. You should not make up for missed doses.

Can I use minoxidil topical solution 2% more than two times a day?

Will it work faster, better?

No. Minoxidil topical solution 2% will not work faster or better if used more than two times a day. Studies have been carefully conducted to determine the correct amount of minoxidil topical solution 2% needed to get the best results. More frequent use or larger doses have not been shown to speed up hair growth and may increase your chances of side effects.

What are the most common side effects with minoxidil topical solution 2%?

The most common side effects are itching and other skin irritations of the treated area of the scalp. Minoxidil topical solution 2% contains alcohol, which would cause burning or irritation of the eyes or sensitive skin areas. If minoxidil topical solution 2% accidentally gets into these areas, rinse with large amounts of cool tap water. Contact your doctor if irritation persists.

What kind of shampoo should I use with minoxidil topical solution 2%?

If you wash your scalp before applying minoxidil topical solution 2%, use a mild shampoo.

Can I use hair sprays, mousses, conditioners, gels, etc.?

Yes. There is no need to change your usual hair care routine when using minoxidil topical solution 2%. However, you should apply minoxidil topical solution 2% first and wait for it to dry before applying your styling aids.

Can I have my hair colored or permed or use hair relaxers while using minoxidil topical solution 2%?

Yes. We have no information that these treatments change the effect of minoxidil topical solution 2%. However, to avoid possible scalp irritation, you should make sure all of the minoxidil topical solution 2% has been washed off the hair and scalp before using these chemicals.

Can I apply minoxidil topical solution 2% and wash my hair an hour later?

No. For minoxidil topical solution 2% to work best, you should allow minoxidil topical solution 2% to remain on the scalp for about 4 hours before washing.

Can I go swimming or out in the rain?

Yes. Avoid washing off the minoxidil topical solution 2%. If possible, apply minoxidil topical solution 2% to a dry scalp after swimming, or wait about 4 hours after application before going swimming. Do not let your scalp get wet from the rain after applying minoxidil topical solution 2%.

Can minoxidil topical solution 2% produce unwanted hair?

Although unwanted hair growth has been reported on the face and on other parts of the body, such reports have been infrequent. The unwanted hair growth may be caused by the transfer of minoxidil topical solution 2% to areas other than the scalp, or by absorption into the circulatory system of low levels of the active ingredient, or by a medical condition not related to the use of minoxidil topical solution 2%.

If you experience unwanted hair, discontinue using minoxidil topical solution 2% and see your doctor for recommendations about appropriate treatment. After stopping use of minoxidil topical solution 2%, the unwanted hair, if caused by the use of minoxidil topical solution 2%, should go away over time.

You can take steps to decrease the chances for unwanted hair growth:

1) limit the application of minoxidil topical solution 2% only to the scalp,

2) if you use your hands to apply minoxidil topical solution 2%, wash your hands thoroughly afterwards, and

3) allow sufficient drying time (usually 2 to 4 hours before going to bed) after your nighttime application of minoxidil topical solution 2%.

Can I use minoxidil topical solution 2% for baldness or hair loss in babies and children?

No. Minoxidil topical solution 2% must not be used to treat baldness or hair loss in babies or children.

Are there any special warnings about the use of minoxidil topical solution 2%?

For external use only

Flammable: Keep away from fire or flame

Do not use if

- your degree of hair loss is more than that shown on the other side of this leaflet, because this product may not work for you
- you have no family history of hair loss
- your hair loss is sudden and/or patchy
- your hair loss is associated with childbirth
- you do not know the reason for your hair loss
- you are under 18 years of age. Do not use on babies and children.
- your scalp is red, inflamed, infected, irritated, or painful
- you use other medicines on the scalp

Ask a doctor before use if you have heart disease.

When using this product

- do not apply on other parts of the body
- avoid contact with the eyes. In case of accidental contact, rinse eyes with large amounts of cool tap water.
- some people have experienced changes in hair color and/or texture
- it takes time to regrow hair. You may need to use this product 2 times a day for at least 4 months before you see results.
- the amount of hair regrowth is different for each person. This product will not work for everyone.

Stop use and ask a doctor if

- chest pain, rapid heartbeat, faintness, or dizziness occurs
- scalp irritation or redness occurs
- sudden, unexplained weight gain occurs
- unwanted facial hair growth occurs
- your hands or feet swell
- you do not see hair regrowth in 4 months

May be harmful if used when pregnant or breast-feeding.

Keep out of reach of children.

If swallowed, get medical help or contact a Poison Control Center right away. (1-800-222-1222)

What factors may increase the risk of serious side effects with minoxidil topical solution 2%?

Minoxidil topical solution 2% should be applied only to the scalp. The risk of side effects may be greater when it is applied to other parts of the body.

Directions for Use

1) Remove the cap. To remove, push down and turn in direction of the arrows on the cap.

2) Part your hair in the area of hair thinning/loss. Follow the instructions below for using the dropper applicator and apply one mL 2 times a day directly onto the scalp in the hair loss area. Do not use more. Spread the liquid evenly over the hair loss area. If you use your fingers, wash hands with soap and water immediately. Each bottle should last about one month, if used as directed. Use a mild shampoo if you wash your scalp before applying minoxidil topical solution 2%.

Using the Dropper Applicator

1) Squeeze the rubber bulb and insert the dropper into the bottle. Release the bulb, allowing the dropper to fill to the 1 mL line. If the level of the solution is above the 1 mL line, squeeze the extra amount back into the bottle.

2) Next, place the tip of the dropper near the part of the scalp you want to treat and gently squeeze the bulb to gradually release the solution. To prevent the solution from running off the scalp, apply a small amount at a time.

3) After each use attach the dropper to the bottle to make it child-resistant by turning it clockwise until tightly closed.

If you have any other questions, ask your health care professional or call 1-800-719-9260.

Store at 20º to 25ºC (68º to 77ºF)

Keep tightly closed.

Save this leaflet for future reference.

Packaged by

Perrigo®

Allegan, MI 49010

Rev 01-20

77A0000J1

Package/Label Principal Display Panel

#1 Dermatologist Recommended Active Ingredient

meijer®

WOMEN’S MINOXIDIL TOPICAL SOLUTION USP, 2%

hair regrowth treatment

REACTIVATES HAIR FOLLICLES TO STIMULATE REGROWTH

CLINICALLY PROVEN TO HELP REGROW HAIR

UNSCENTED | TOPICAL SOLUTION

FOR WOMEN

Compare to Women’s Rogaine® Active Ingredient

3 MONTH SUPPLY

3 BOTTLES

2 FL OZ (60 mL) EACH